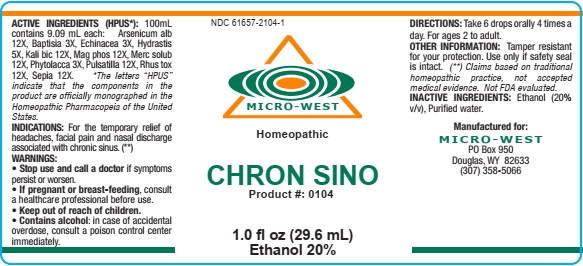 DRUG LABEL: CHRON SINO
NDC: 61657-2104 | Form: LIQUID
Manufacturer: White Manufacturing Inc. DBA Micro-West
Category: homeopathic | Type: HUMAN OTC DRUG LABEL
Date: 20210121

ACTIVE INGREDIENTS: ARSENIC TRIOXIDE 12 [hp_X]/30 mL; BAPTISIA TINCTORIA ROOT 3 [hp_X]/30 mL; ECHINACEA ANGUSTIFOLIA 3 [hp_X]/30 mL; GOLDENSEAL 5 [hp_X]/30 mL; POTASSIUM DICHROMATE 12 [hp_X]/30 mL; MAGNESIUM PHOSPHATE, DIBASIC TRIHYDRATE 12 [hp_X]/30 mL; MERCURIUS SOLUBILIS 12 [hp_X]/30 mL; PHYTOLACCA AMERICANA ROOT 3 [hp_X]/30 mL; ANEMONE PULSATILLA 12 [hp_X]/30 mL; TOXICODENDRON PUBESCENS LEAF 12 [hp_X]/30 mL; SEPIA OFFICINALIS JUICE 12 [hp_X]/30 mL
INACTIVE INGREDIENTS: ALCOHOL; WATER

CHRON SINO

ACTIVE INGREDIENTS (HPUS*): 100mL
contains 9.09 mL each: Arsenicum alb
12X, Baptisia 3X, Echinacea 3X, Hydrastis
5X, Kali bic 12X, Mag phos 12X, Merc solub
12X, Phytolacca 3X, Pulsatilla 12X, Rhus tox
12X, Sepia 12X. *The letters “HPUS”
indicate that the components in the
product are officially monographed in the
Homeopathic Pharmacopeia of the United
States.

INDICATIONS: For the temporary relief of
headaches, facial pain and nasal discharge
associated with chronic sinus. (**)

WARNINGS:
• Stop use and call a doctor if symptoms
persist or worsen.
• If pregnant or breast-feeding, consult
a healthcare professional before use.
• Keep out of reach of children.
• Contains alcohol: in case of accidental
overdose, consult a poison control center
immediately.

• Keep out of reach of children.

DOSAGE AND ADMINISTRATION

DIRECTIONS: Take 6 drops orally 4 times a
day. For ages 2 to adult.

OTHER INFORMATION: Tamper resistant
for your protection. Use only if safety seal
is intact. (**) Claims based on traditional
homeopathic practice, not accepted
medical evidence. Not FDA evaluated.

INACTIVE INGREDIENTS: Ethanol (20%
v/v), Purified water.

QUESTIONS

Manufactured for:
MICRO-WEST
PO Box 950
Douglas, WY 82633
(307) 358-5066

PACKAGE LABEL

NDC 61657-2104-1

MICRO-WEST

Homeopathic

CHRON SINO

Product #: 0104

1.0 fl oz (29.6 mL)

Ethanol 20%

PURPOSE

For the temporary relief of
headaches, facial pain and nasal discharge
associated with chronic sinus. (**)